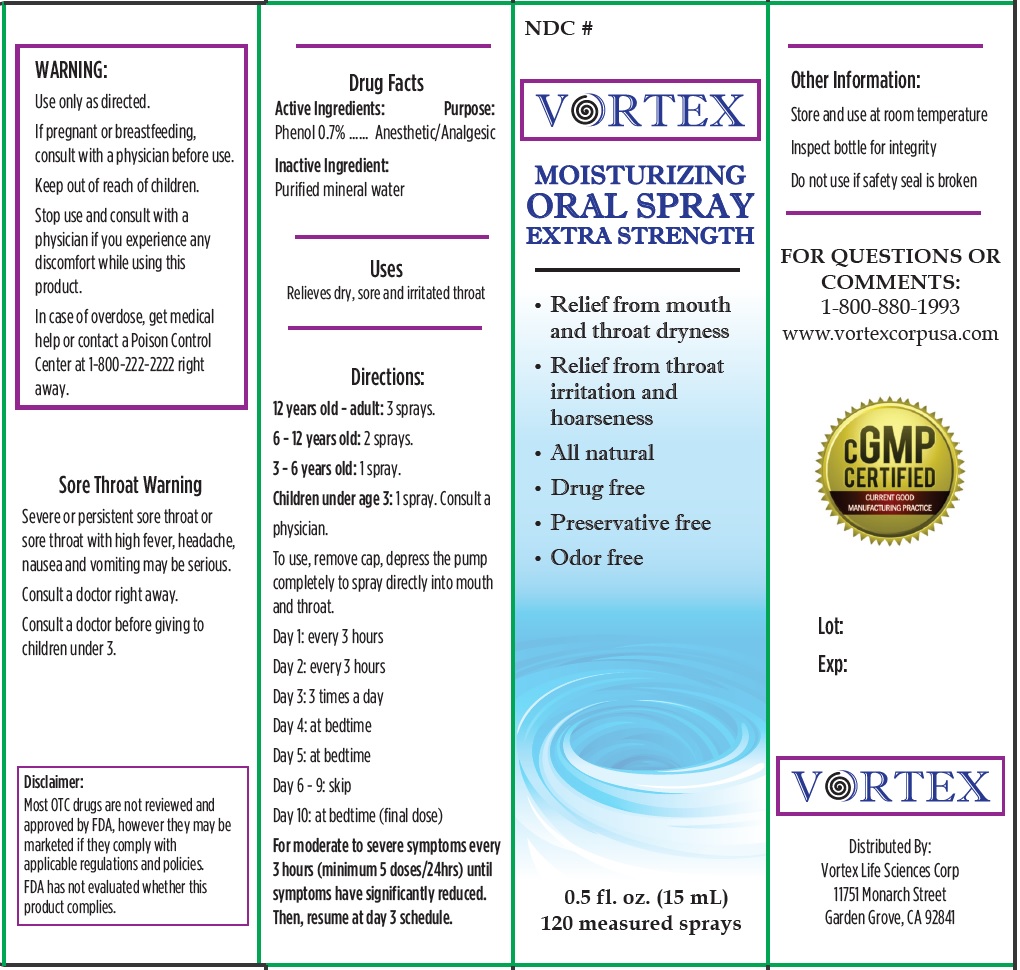 DRUG LABEL: Vortex Moisturizer Oral
NDC: 82529-001 | Form: SPRAY
Manufacturer: Vortex Life Sciences, Inc.
Category: otc | Type: HUMAN OTC DRUG LABEL
Date: 20220307

ACTIVE INGREDIENTS: PHENOL 7 mg/1 mL
INACTIVE INGREDIENTS: WATER

Vortex Moisturizer Oral Spray

Active Ingredients:

Phenol 0.7%

Purpose:

Anesthetic/Analgesic

Inactive Ingredient:

Purified mineral water

Uses

Relieves dry, sore and irritated throat

Directions:

12 years old - adult: 3 sprays.
6 - 12 years old: 2 sprays.
3 - 6 years old: 1 spray.
Children under age 3: 1 spray. Consult a
physician.
To use, remove cap, depress the pump
completely to spray directly into mouth
and throat.
Day 1: every 3 hours
Day 2: every 3 hours
Day 3: 3 times a day
Day 4: at bedtime
Day 5: at bedtime
Day 6 - 9: skip
Day 10: at bedtime (final dose)
For moderate to severe symptoms every 3 hours (minimum 5 doses/24hrs) until symptoms have significantly reduced. Then, resume at day 3 schedule.

WARNING:

Use only as directed.

If pregnant or breastfeeding,

consult with a physician before use.

Stop use and consult with a physician

if you experience any discomfort while using this product.

In case of overdose, get medical help or contact a Poison Control Center at 1-800-222-2222 right away.

Sore Throat Warning

Severe or persistent sore throat or sore throat with high fever, headache, nausea and vomiting may be serious. Consult a doctor right away. Consult a doctor before giving to children under 3.

Other Information:

Store and use at room temperature Inspect bottle for integrity Do not use if safety seal is broken